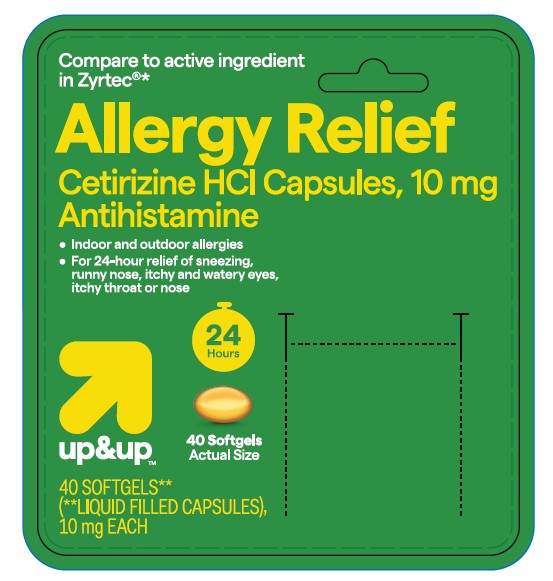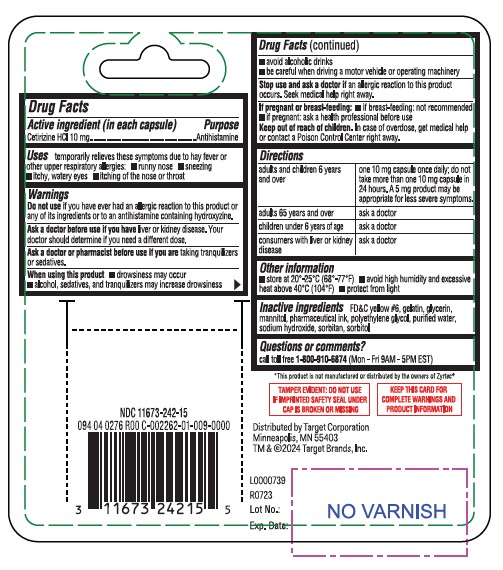 DRUG LABEL: Cetirizine HCl
NDC: 11673-242 | Form: CAPSULE
Manufacturer: TARGET Corporation
Category: otc | Type: HUMAN OTC DRUG LABEL
Date: 20251216

ACTIVE INGREDIENTS: CETIRIZINE HYDROCHLORIDE 10 mg/1 1
INACTIVE INGREDIENTS: FD&C YELLOW NO. 6; GELATIN; GLYCERIN; MANNITOL; POLYETHYLENE GLYCOL, UNSPECIFIED; WATER; SODIUM HYDROXIDE; SORBITAN; SORBITOL

Drug Facts

Active ingredient (in each capsule)

Cetirizine HCl 10 mg

Purpose

Antihistamine

Uses

temporarily relieves these symptoms due to hay fever or other upper respiratory allergies:

- runny nose
- sneezing
- itchy, watery eyes
- itching of the nose or throat

Warnings

Do not use

if you have ever had an allergic reaction to this product or any of its ingredients or to an antihistamine containing hydroxyzine.

Ask a doctor before use if you have

liver or kidney disease. Your doctor should determine if you need a different dose.

Ask a doctor or pharmacist before use if you are

taking tranquilizers or sedatives.

When using this product

- drowsiness may occur
- alcohol, sedatives, and tranquilizers may increase drowsiness
- avoid alcoholic drinks
- be careful when driving a motor vehicle or operating machinery

Stop use and ask a doctor if

an allergic reaction to this product occurs. Seek medical help right away.

If pregnant or breast-feeding:

- if breast-feeding: not recommended
- if pregnant: ask a health professional before use

Keep out of reach of children.

In case of overdose, get medical help or contact a Poison Control Center right away.

Directions

adults and children 6 years and over | one 10 mg capsule once daily; do not take more than one 10 mg capsule in 24 hours. A 5 mg product may be appropriate for less severe symptoms.
adults 65 years and over | ask a doctor
children under 6 years of age | ask a doctor
consumers with liver or kidney disease | ask a doctor

Other Information

- store at 20º-25ºC (68º-77ºF)
- avoid high humidity and excessive heat above 40ºC (104ºF)
- protect from light

Inactive ingredients

FD&C yellow #6, gelatin, glycerin, mannitol, pharmaceutical ink, polyethylene glycol, purified water, sodium hydroxide, sorbitan, sorbitol

Questions?

call 1-800-910-6874

*All trademarks are property of their respective owners. This product is not affiliated with the makers/owners of Zyrtec®.

TAMPER EVIDENT: DO NOT USE IF IMPRINTED SAFETY SEAL UNDER CAP IS BROKEN OR MISSING

KEEP THIS CARD FOR COMPLETE WARNINGS AND PRODUCT INFORMATION

Dist. by Target Corp., Mpls., MN 55403

TM & ©2024 Target Brands, Inc.

L0000739

R0723

Principal Display Panel

NDC 11673-242-15

Compare to active ingredient in Zyrtec®*

allergy relief

cetirizine HCl capsules, 10 mg antihistamine

indoor and outdoor allergies

24 hour relief of:
• sneezing
• runny nose
• itchy, watery eyes
• itchy throat or nose

24HOUR RELIEF

ACTUAL SIZE

40SOFTGELS**

up & upTM

40 SOFTGELS**(**LIQUID-FILLED CAPSULES)
10 mg EACH

front

back